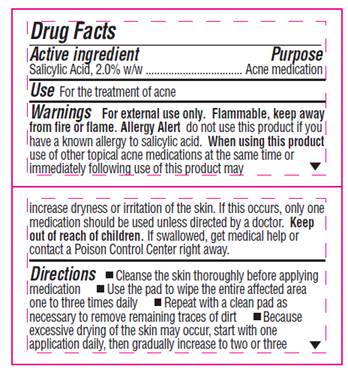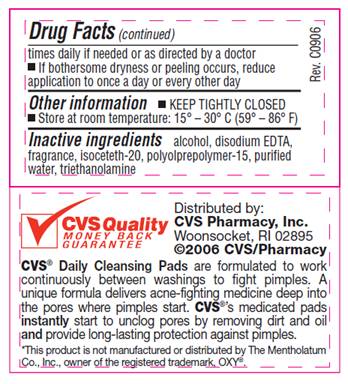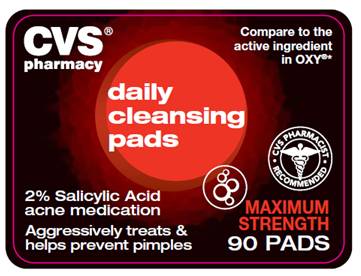 DRUG LABEL: Daily Cleansing
NDC: 50730-7801 | Form: SWAB
Manufacturer: H and P Industries, Inc. dba Triad Group
Category: otc | Type: HUMAN OTC DRUG LABEL
Date: 20091228

ACTIVE INGREDIENTS: SALICYLIC ACID 0.02 mL/1 1
INACTIVE INGREDIENTS: ALCOHOL; EDETATE DISODIUM; WATER; TROLAMINE

DRUG FACTS

ACTIVE INGREDIENT

Salicylic acid 2.0% w/w

PURPOSE

Acne medication

USE

for the treatment of acne

WARNINGS

For external use only. Flammable, keep away from fire or flame.

Allergy alert

do not use this product if you have a known allergy to salicylic acid.

When using this product

use of other topical acne medications at the same time or immediately following use of this product may increase dryness or irritation of the skin. If this occurs, only one medication should be used unless directed by a doctor.

Keep out of reach of children

If swallowed, get medical help or contact a Poison Control Center right away.

DIRECTIONS

- Cleanse the skin thoroughly before applying medication
- Use the pad to wipe the entire affected area one to three times daily
- Repeat with a clean pad as necessary to remove remaining traces of dirt
- Because excessive drying of the skin may occur, start with one application daily, then gradually increase to two or three times daily if needed or as directed by a doctor
- If bothersome dryness of peeling occurs, reduce application to once a day or every other day

OTHER INFORMATION

- KEEP TIGHTLY CLOSED
- Store at room temperature: 15°- 30° C (59° - 86° F)

INACTIVE INGREDIENTS

alcohol, disodium EDTA, fragrance, isoceteth-20, polyolprepolymer-15, purified water, triethalnolamine

LABEL INFORMATION - REPRESENTATIVE LABEL

Compare to the active ingredient in Oxy®*

Daily Cleansing Pads

2% Salicylic Acid acne medication

Aggressively treats and helps prevent pimples

MAXIMUM STRENGTH
90 PADS

*This product is not manufactured or distributed by The Mentholatum Co. Inc., owner of the registered trademark, OXY®.